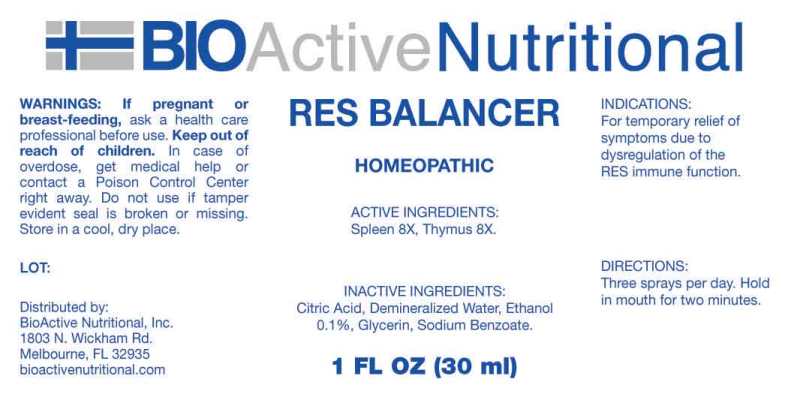 DRUG LABEL: Res Balancer
NDC: 43857-0287 | Form: SPRAY
Manufacturer: BioActive Nutritional, Inc.
Category: homeopathic | Type: HUMAN OTC DRUG LABEL
Date: 20211209

ACTIVE INGREDIENTS: BOS TAURUS SPLEEN 8 [hp_X]/1 mL; BOS TAURUS THYMUS 8 [hp_X]/1 mL
INACTIVE INGREDIENTS: CITRIC ACID MONOHYDRATE; GLYCERIN; SODIUM BENZOATE; WATER; ALCOHOL

Drug Facts:

ACTIVE INGREDIENTS:

Spleen (Bovine) 8X, Thymus (Bovine) 8X.

INDICATIONS:

For temporary relief of symptoms due to dysregulation of the RES immune function.

WARNINGS:

If pregnant or breast-feeding, ask a health care professional before use.

Keep out of reach of children. In case of overdose, get medical help or contact a Poison Control Center right away.

Do not use if tamper evident seal is broken or missing.

Store in cool, dry place.

Keep out of reach of children. In case of overdose, get medical help or contact a Poison Control Center right away.

DIRECTIONS:

Three sprays per day. Hold in mouth for two minutes.

INDICATIONS:

For temporary relief of symptoms due to dysregulation of the RES immune function.

INACTIVE INGREDIENTS:

Citric Acid, Demineralized Water, Ethanol 0.1%, Glycerin, Sodium Benzoate

QUESTIONS:

Distributed by:
BioActive Nutritional, Inc.
1803 N. Wickham Rd.
Melbourne, FL 32935
bioactivenutritional.com

PACKAGE LABEL DISPLAY

BIOActive Nutritional

RES BALANCER

HOMEOPATHIC

1 FL OZ (30 ml)